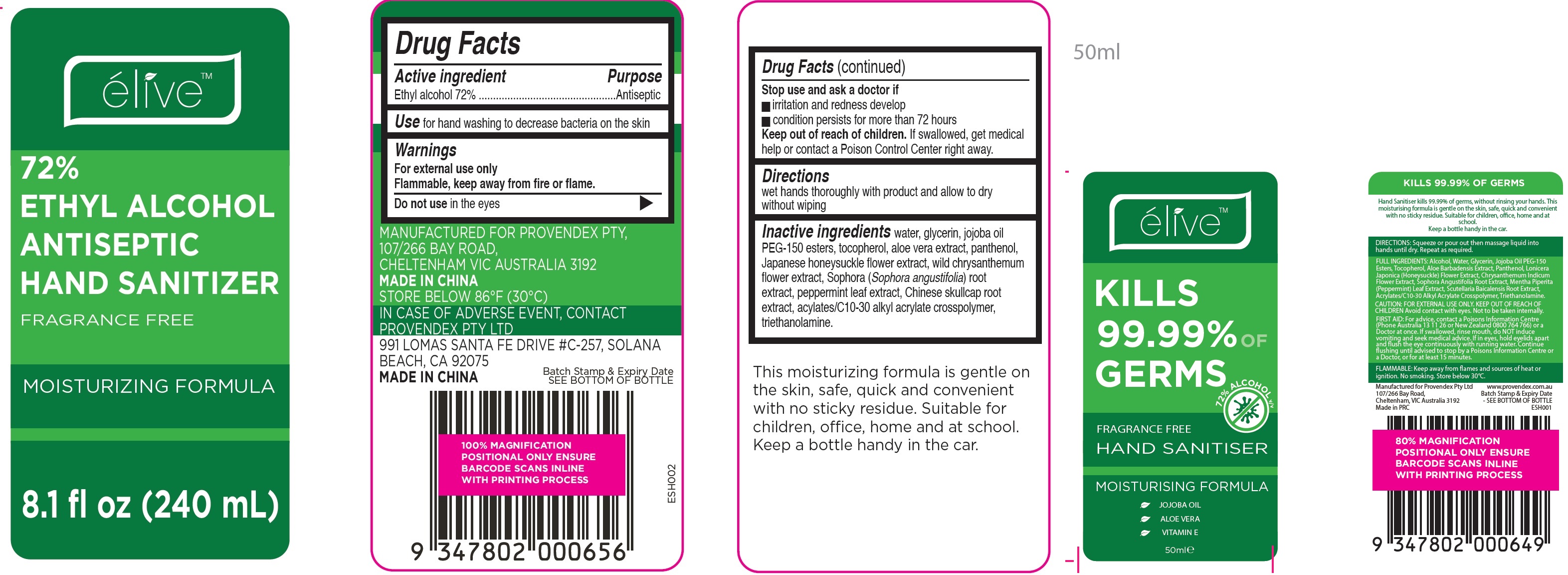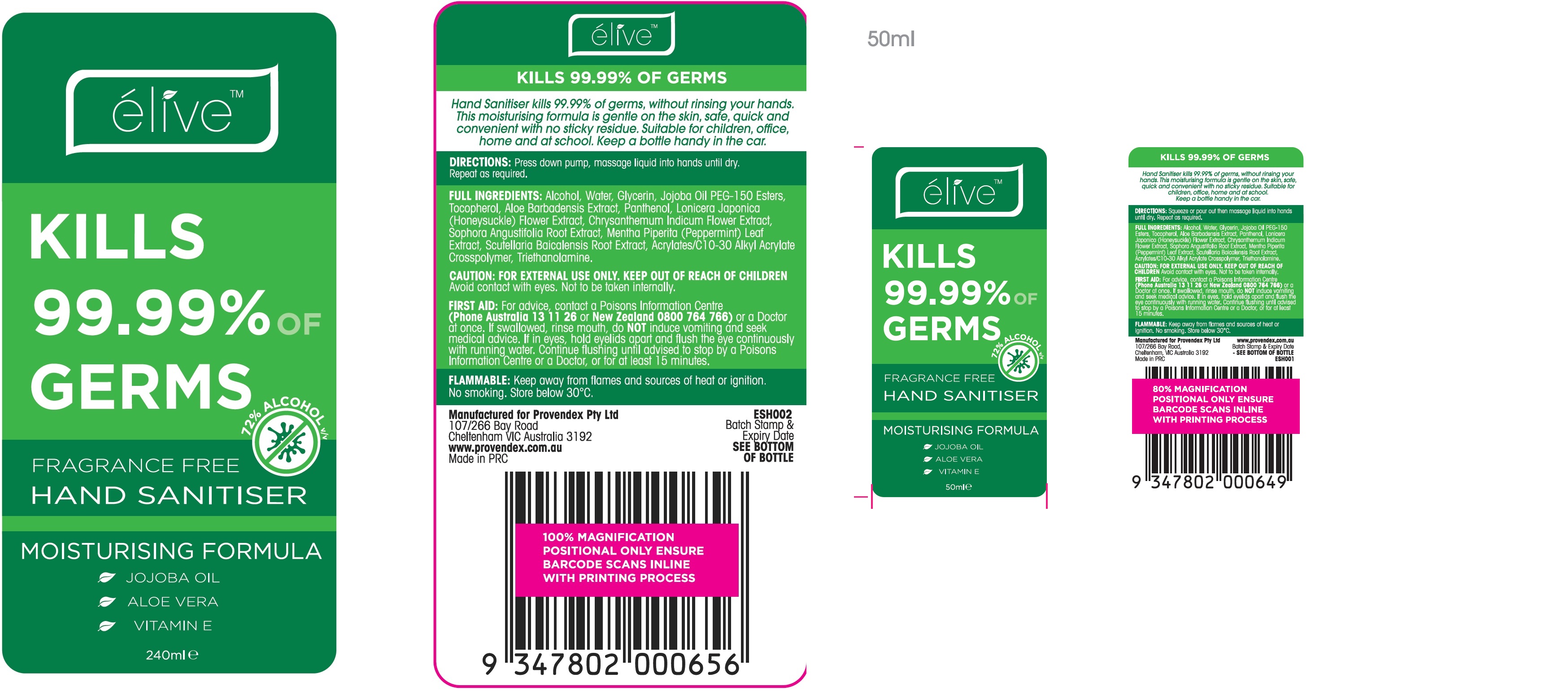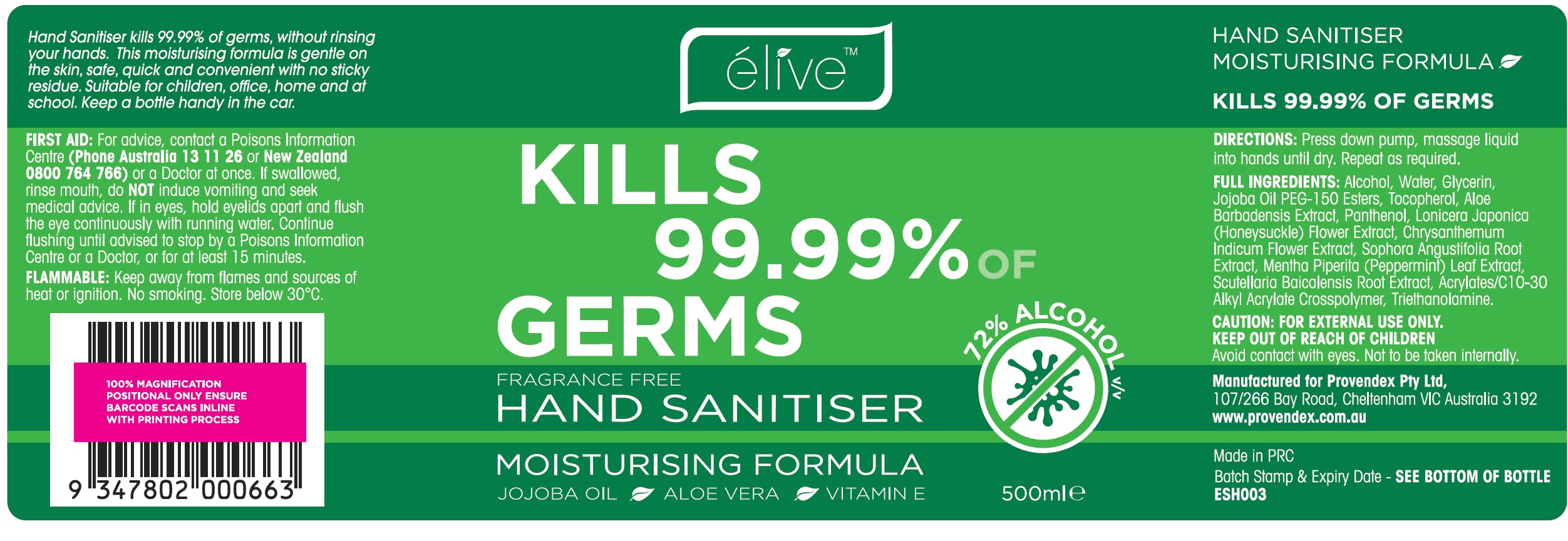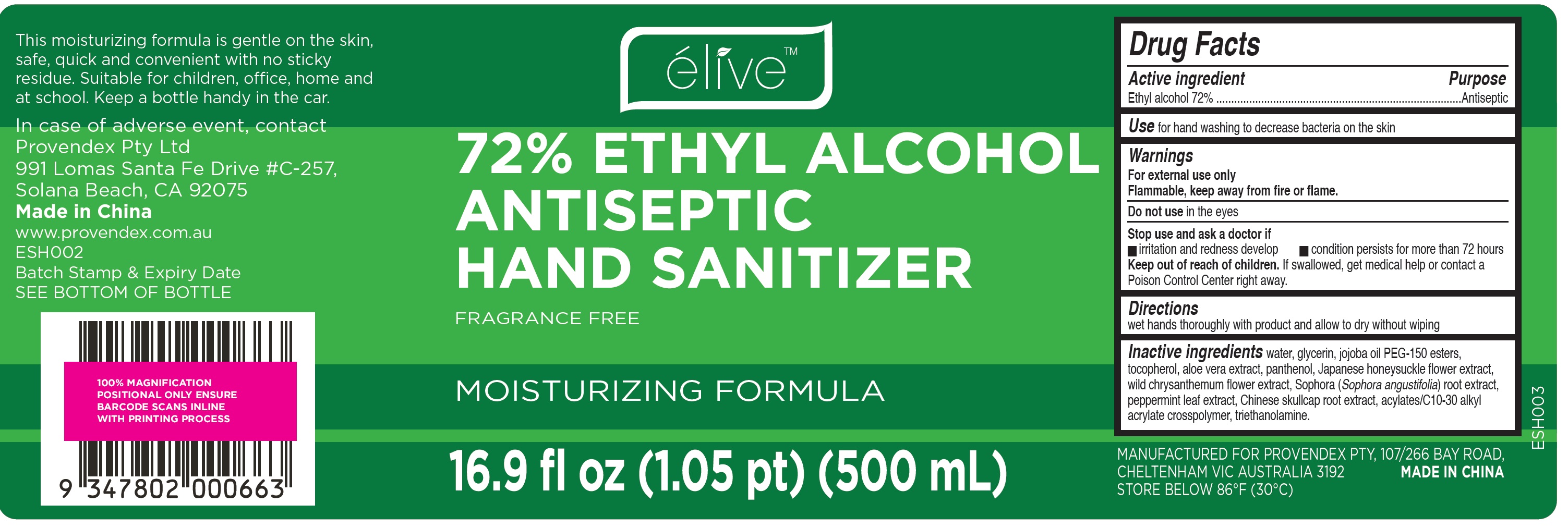 DRUG LABEL: ELIVE Hand Sanitizer
NDC: 79123-000 | Form: GEL
Manufacturer: Provendex Pty Ltd
Category: otc | Type: HUMAN OTC DRUG LABEL
Date: 20200707

ACTIVE INGREDIENTS: ALCOHOL 0.72 mL/1 mL
INACTIVE INGREDIENTS: WATER; GLYCERIN; JOJOBA OIL; TOCOPHEROL; ALOE VERA LEAF; PANTHENOL; SOPHORA FLAVESCENS ROOT; CHRYSANTHEMUM INDICUM FLOWER; MENTHA PIPERITA LEAF; TROLAMINE

ELIVE Hand Sanitizer

Active ingredient

Ethyl alcohol 72%

Purpose

Antiseptic

Use

for hand washing to decrease bacteria on the skin

Warnings

For external use only
Flammable, keep away from fire or flame.

Do not use

in the eyes

Stop use and ask a doctor if

- irritation and redness develop
- condition persists for more than 72 hours

Keep out of reach of children.

If swallowed, get medical help or contact a Poison Control Center right away.

Directions

wet hands thoroughly with product and allow to dry without wiping

Inactive ingredients

water, glycerin, jojoba oil PEG-150 esters, tocopherol, aloe vera extract, panthenol, Japanese honeysuckle flower extract, wild chrysanthemum flower extract, Sophora (Sophora angustifolia) root extract, peppermint leaf extract, Chinese skullcap root extract, acylates/C10-30 alkyl acrylate crosspolymer, triethanolamine.